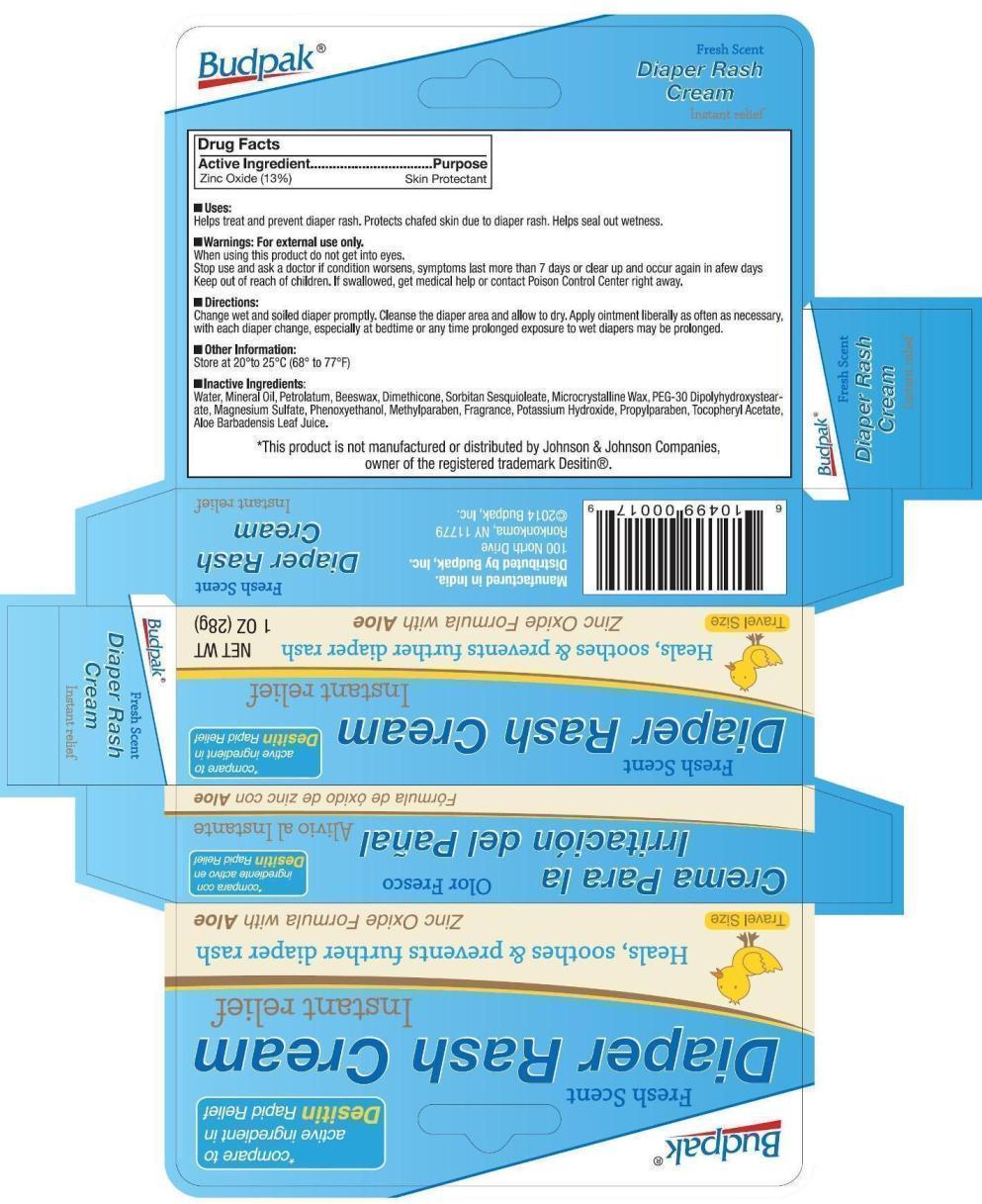 DRUG LABEL: Budpak Diaper Rash
NDC: 27293-028 | Form: CREAM
Manufacturer: Budpak Inc. 
Category: otc | Type: HUMAN OTC DRUG LABEL
Date: 20140214

ACTIVE INGREDIENTS: ZINC OXIDE 13 g/100 g
INACTIVE INGREDIENTS: WATER; MINERAL OIL; PETROLATUM; YELLOW WAX; DIMETHICONE; SORBITAN SESQUIOLEATE; MICROCRYSTALLINE WAX; PEG-30 DIPOLYHYDROXYSTEARATE; MAGNESIUM SULFATE; PHENOXYETHANOL; METHYLPARABEN; POTASSIUM HYDROXIDE; PROPYLPARABEN; .ALPHA.-TOCOPHEROL ACETATE; ALOE VERA LEAF

Budpak Diaper Rash Cream

Active Ingredient

Zinc Oxide 13%

Purpose

Skin Protectant

Uses

Helps treat and prevent diaper rash. Protects chafed skin due to diaper rash. Helps seal out wetness

Warnings

For external use only

When using this product do not get into eyes

Stop use and ask a doctor if condition worsens, symptoms last more than 7 days or clear up and occur again in few days.

Keep out of reach of children.

If swallowed, get medical help or contact Poison Control Center right away.

Directions

Change wet or soiled diapers promptly. Cleanse the diaper area and allow to dry. Apply ointment liberally as often as necessary, with each diaper change, especially at bedtime or any time prolonged exposure to wet diapers may be prolonged.

Other Information

Store at 20°to 25°C (68° to 77°F).

Inactive Ingredients

Water, Mineral Oil, Petrolatum, Beeswax, Dimethicone, Sorbitan Sesquioleate, Microcrystalline Wax, PEG-30 Dipolyhydroxystearate, Magnesium Sulfate, Phenoxyethanol, Methylparaben, Fragrance, Potassium Hydroxide, Propylparaben, Tocopheryl Acetate, Aloe Barbadensis Leaf Juice.

PRINCIPAL DISPLAY PANEL

Budpak Diaper Rash Cream

Zinc Oxide 13%

NET WT 1 OZ (28 g)